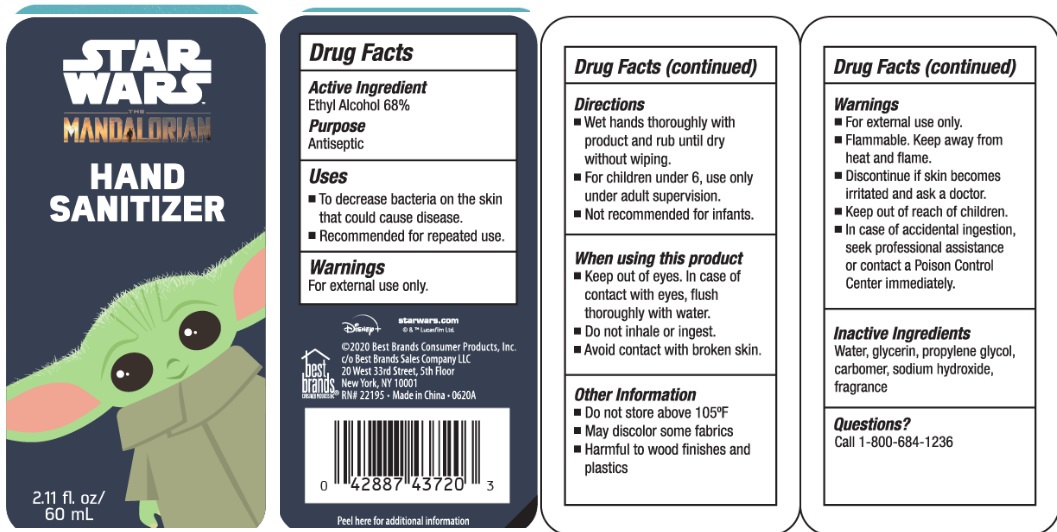 DRUG LABEL: star wars HAND SANITIZER
NDC: 74274-002 | Form: SOLUTION
Manufacturer: Huizhou Bliss Commodity Co., Ltd
Category: otc | Type: HUMAN OTC DRUG LABEL
Date: 20200609

ACTIVE INGREDIENTS: ALCOHOL 68 mL/100 mL
INACTIVE INGREDIENTS: WATER; CARBOMER INTERPOLYMER TYPE A (ALLYL SUCROSE CROSSLINKED); GLYCERIN; PROPYLENE GLYCOL; SODIUM HYDROXIDE

Active ingredient

Ethyl Alcohol 68%

Purpose

Antiseptic

Use

- Decreases bacteria on the skin that could cause disease.
- Recommended for repeated use.

Warnings

- For external use only.
- Flammable.Keep product away from heat or flame.
- Discontinue if skin becomes irritated and ask a doctor
- Keep out of reach of children.
- In case of accidental ingestion seek professional assistance or contact a Poison Control Center immediately.

Keep out of reach of children.

If swallowed, get medical help or contact a Poison Control Center right away.

Directions

- Wet hands thoroughly with product and rub until dry without wiping.
- For children under 6, use only under adult supervison.
- Not recommended for infants.

Inactive ingredients

Water, glycerin, propyene glycol, carbomer, sodium hydroxide, fragrance

other information:

- Do not store above 105 Fahrenheit degree
- May discolor some fabrics
- Harmful to wood finishes and plastics